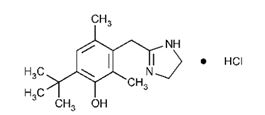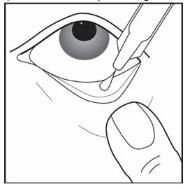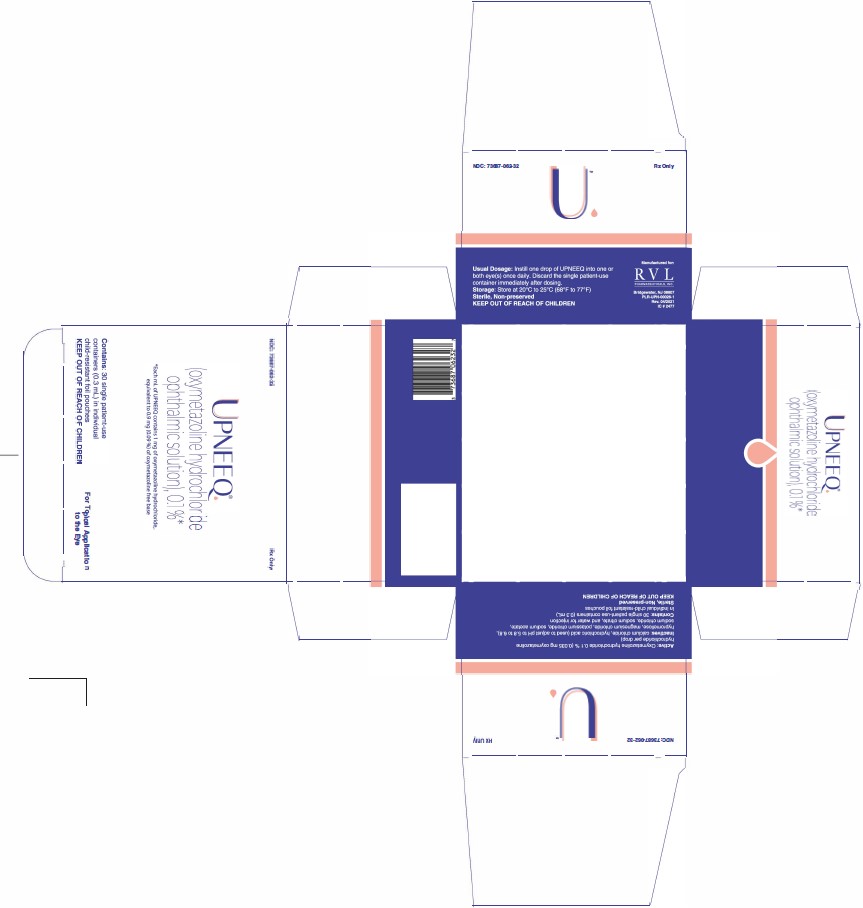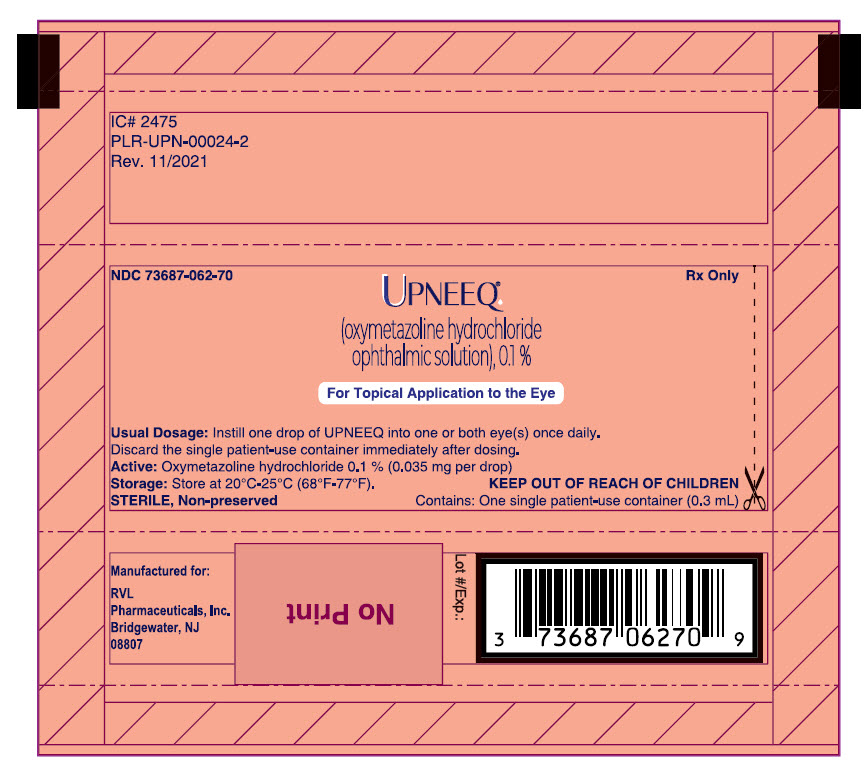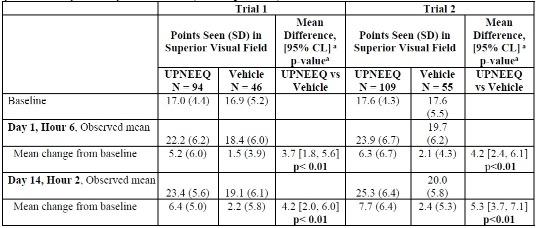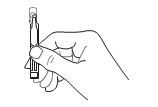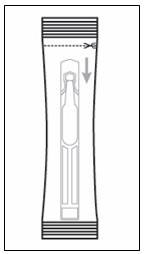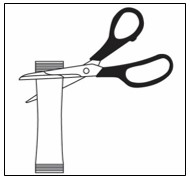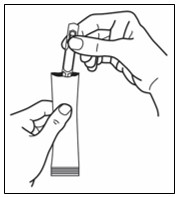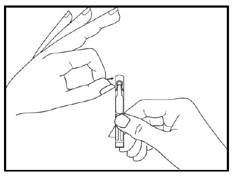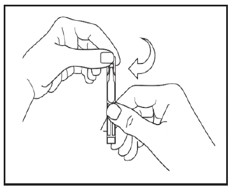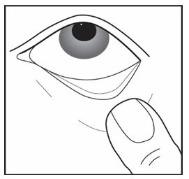 DRUG LABEL: UPNEEQ
NDC: 73687-062 | Form: SOLUTION/ DROPS
Manufacturer: RVL Pharmaceuticals, Inc.
Category: prescription | Type: HUMAN PRESCRIPTION DRUG LABEL
Date: 20250919

ACTIVE INGREDIENTS: OXYMETAZOLINE HYDROCHLORIDE 1 mg/1 mL
INACTIVE INGREDIENTS: CALCIUM CHLORIDE; HYPROMELLOSE, UNSPECIFIED; MAGNESIUM CHLORIDE; POTASSIUM CHLORIDE; SODIUM ACETATE; SODIUM CHLORIDE; SODIUM CITRATE; HYDROCHLORIC ACID; WATER

HIGHLIGHTS OF PRESCRIBING INFORMATION

These highlights do not include all the information needed to use UPNEEQ® safely and effectively. See full prescribing information for UPNEEQ.
UPNEEQ (oxymetazoline hydrochloride ophthalmic solution), 0.1%, for topical ophthalmic use
Initial U.S. Approval: 1964

1 INDICATIONS AND USAGE

UPNEEQ is indicated for the treatment of acquired blepharoptosis in adults. (1)

2 DOSAGE AND ADMINISTRATION

Instill one drop into one or both ptotic eye(s) once daily. (2)

3 DOSAGE FORMS AND STRENGTHS

Ophthalmic solution, 0.1% oxymetazoline as salt, equivalent to 0.09% oxymetazoline as base. (3)

4 CONTRAINDICATIONS

None. (4)

5 WARNINGS AND PRECAUTIONS

- Ptosis may be associated with neurologic or orbital diseases such as stroke and/or cerebral aneurysm, Horner syndrome, myasthenia gravis, external ophthalmoplegia, orbital infection and orbital masses. Consideration should be given to these conditions in the presence of ptosis with decreased levator muscle function and/or other neurologic signs. (5.1)
- Alpha-adrenergic agonists as a class may impact blood pressure. Advise patients with cardiovascular disease, orthostatic hypotension, and/or uncontrolled hypertension or hypotension to seek medical care if their condition worsens. (5.2)
- Use with caution in patients with cerebral or coronary insufficiency or Sjögren’s syndrome and advise patients to seek medical care if signs and symptoms of potentiation of vascular insufficiency develop. (5.3)
- Advise patients to seek immediate medical care if pain, redness, blurred vision and photophobia occur (signs and symptoms of acute angle closure). (5.4)

6 ADVERSE REACTIONS

Most common adverse reactions (incidence 1-5%) are: punctate keratitis, conjunctival hyperemia, dry eye, vision blurred, instillation site pain, eye irritation and headache. (6.1)

To report SUSPECTED ADVERSE REACTIONS, contact RVL Pharmaceuticals, Inc. at 1-877-482-3788 or FDA at 1-800-FDA-1088 or www.fda.gov/medwatch.

FULL PRESCRIBING INFORMATION

1 INDICATIONS AND USAGE

UPNEEQ is indicated for the treatment of acquired blepharoptosis in adults.

2 DOSAGE AND ADMINISTRATION

Instill one drop of UPNEEQ into one or both ptotic eye(s) once daily. Discard the single patient-use container immediately after dosing.

Contact lenses should be removed prior to instillation of UPNEEQ and may be reinserted 15 minutes following its administration.

If more than one topical ophthalmic drug is being used, the drugs should be administered at least 15 minutes between applications.

3 DOSAGE FORMS AND STRENGTHS

UPNEEQ (oxymetazoline hydrochloride ophthalmic solution), 0.1%, equivalent to 0.09% as oxymetazoline base, is formulated for topical ocular delivery as a sterile, non-preserved, clear, colorless to slightly yellow ophthalmic solution.

4 CONTRAINDICATIONS

None.

5 WARNINGS AND PRECAUTIONS

5.1 Ptosis as Presenting Sign of Serious Neurologic Disease

Ptosis may be associated with neurologic or orbital diseases such as stroke and/or cerebral aneurysm, Horner syndrome, myasthenia gravis, external ophthalmoplegia, orbital infection and orbital masses. Consideration should be given to these conditions in the presence of ptosis with decreased levator muscle function and/or other neurologic signs.

5.2 Potential Impacts on Cardiovascular Disease

Alpha-adrenergic agonists may impact blood pressure. UPNEEQ should be used with caution in patients with severe or unstable cardiovascular disease, orthostatic hypotension, and uncontrolled hypertension or hypotension. Advise patients with cardiovascular disease, orthostatic hypotension, and/or uncontrolled hypertension/hypotension to seek immediate medical care if their condition worsens.

5.3 Potentiation of Vascular Insufficiency

UPNEEQ should be used with caution in patients with cerebral or coronary insufficiency, or Sjögren’s syndrome. Advise patients to seek immediate medical care if signs and symptoms of potentiation of vascular insufficiency develop.

5.4 Risk of Angle Closure Glaucoma

UPNEEQ may increase the risk of angle closure glaucoma in patients with untreated narrow-angle glaucoma. Advise patients to seek immediate medical care if signs and symptoms of acute angle closure glaucoma develop.

5.5 Risk of Contamination

Patients should not touch the tip of the single patient-use container to their eye or to any surface, in order to avoid eye injury or contamination of the solution.

6 ADVERSE REACTIONS

6.1 Clinical Trials Experience

Because clinical trials are conducted under widely varying conditions, adverse reaction rates observed in the clinical trials of a drug cannot be directly compared to rates in the clinical trials of another drug and may not reflect the rates observed in practice.

A total of 360 subjects with acquired blepharoptosis were treated with UPNEEQ once daily in each eye for at least 6 weeks in three controlled Phase 3 clinical trials, including 203 subjects treated with UPNEEQ for 6 weeks and 157 subjects treated with UPNEEQ for 12 weeks. Adverse reactions that occurred in 1-5% of subjects treated with UPNEEQ were punctate keratitis, conjunctival hyperemia, dry eye, blurred vision, instillation site pain, eye irritation and headache.

7 DRUG INTERACTIONS

7.1 Anti-hypertensives/Cardiac Glycosides

Alpha-adrenergic agonists, as a class, may impact blood pressure. Caution in using drugs such as beta-blockers, anti-hypertensives, and/or cardiac glycosides is advised.

Caution should also be exercised in patients receiving alpha adrenergic receptor antagonists such as in the treatment of cardiovascular disease, or benign prostatic hypertrophy.

7.2 Monoamine Oxidase Inhibitors

Caution is advised in patients taking MAO inhibitors which can affect the metabolism and uptake of circulating amines.

8 USE IN SPECIFIC POPULATIONS

8.1 Pregnancy

Risk Summary
There are no available data on UPNEEQ use in pregnant women to inform a drug-associated risk for major birth defects and miscarriage. In animal reproduction studies, there were no adverse developmental effects observed after oral administration of oxymetazoline hydrochloride in pregnant rats and rabbits at systemic exposures up to 7 and 278 times the maximum recommended human ophthalmic dose (MRHOD), respectively, based on dose comparison. [see Data]. The estimated background risks of major birth defects and miscarriage for the indicated population are unknown. All pregnancies have a background risk of birth defect, loss, or other adverse outcomes. In the U.S. general population, the estimated background risk of major birth defects and miscarriage in clinically recognized pregnancies is 2-4% and 15-20%, respectively.

Animal Data
Effects on embryo-fetal development were evaluated in rats and rabbits following oral administration of oxymetazoline hydrochloride during the period of organogenesis. Oxymetazoline hydrochloride did not cause adverse effects to the fetus at oral doses up to 0.2 mg/kg/day in pregnant rats during the period of organogenesis (28 times the MRHOD, on a dose comparison basis). Oxymetazoline hydrochloride did not cause adverse effects to the fetus at oral doses up to 1 mg/kg/day in pregnant rabbits during the period of organogenesis (278 times the MRHOD, on a dose comparison basis). Maternal toxicity, including decreased maternal body weight, was produced at the high dose of 1 mg/kg/day in pregnant rabbits and was associated with findings of delayed skeletal ossification.

In a rat prenatal and postnatal development study, oxymetazoline hydrochloride was orally administered to pregnant rats once daily from gestation day 6 through lactation day 20. Maternal toxicity was produced at the high dose of 0.2 mg/kg/day (28 times the MRHOD, on a dose comparison basis) in pregnant rats and was associated with an increase in pup mortality and reduced pup body weights. Delayed sexual maturation was noted at 0.1 mg/kg/day (14 times the MRHOD, on a dose comparison basis). Oxymetazoline hydrochloride did not have any adverse effects on fetal development at a dose of 0.05 mg/kg/day (7 times the MRHOD, on a dose comparison basis).

8.2 Lactation

Risk Summary
No clinical data are available to assess the effects of oxymetazoline on the quantity or rate of breastmilk production, or to establish the level of oxymetazoline present in human breastmilk post-dose. Oxymetazoline was detected in the milk of lactating rats. The developmental and health benefits of breastfeeding should be considered along with the mother’s clinical need for UPNEEQ and any potential adverse effects on the breastfed child from UPNEEQ.

8.4 Pediatric Use

Safety and effectiveness of UPNEEQ have not been established in pediatric patients under 13 years of age.

8.5 Geriatric Use

Three hundred and fifteen subjects aged 65 years and older received treatment with UPNEEQ (n = 216) or vehicle (n = 99) in clinical trials. No overall differences in safety or effectiveness were observed between subjects 65 years of age and older and younger subjects.

10 OVERDOSAGE

Accidental oral ingestion of topical intended solutions (including ophthalmic solutions and nasal sprays) containing imidazoline derivatives (e.g., oxymetazoline) in children has resulted in serious adverse events requiring hospitalization, including nausea, vomiting, lethargy, tachycardia, decreased respiration, bradycardia, hypotension, hypertension, sedation, somnolence, mydriasis, stupor, hypothermia, drooling, and coma. Keep UPNEEQ out of reach of children.

11 DESCRIPTION

UPNEEQ (oxymetazoline hydrochloride ophthalmic solution), 0.1% contains oxymetazoline hydrochloride, an alpha adrenoceptor agonist. UPNEEQ is an aseptically prepared, sterile, non-preserved ophthalmic solution. The chemical name is 6-tert-Butyl-3-(2-imidazolin-2-ylmethyl)-2,4- dimethylphenol monohydrochloride, and the molecular mass is 296.84. Oxymetazoline HCl is freely soluble in water and ethanol and has a partition coefficient of 0.1 in 1-octanol/water. The molecular formula of oxymetazoline HCl is C16H24N2O∙HCl, and its structural formula is:

Each mL of UPNEEQ (oxymetazoline hydrochloride ophthalmic solution) 0.1% contains 1 mg of oxymetazoline hydrochloride, equivalent to 0.9 mg (0.09%) of oxymetazoline free base. The ophthalmic solution contains the following inactive ingredients: calcium chloride, hydrochloric acid (used to adjust pH to 5.8 to 6.8), hypromellose, magnesium chloride, potassium chloride, sodium acetate, sodium chloride, sodium citrate, and water for injection.

12 CLINICAL PHARMACOLOGY

12.1 Mechanism of Action

Oxymetazoline is an alpha adrenoceptor agonist targeting a subset of adrenoreceptors in Mueller’s muscle of the eyelid.

12.2 Pharmacodynamics

In safety and efficacy studies, Study RVL-1201-201 and Study RVL-1201-202, the pharmacodynamics of UPNEEQ was assessed using an objective photographic measure, marginal reflex distance 1 (MRD1). MRD1 is the distance from the central pupillary light reflex to the central margin of the upper lid. The maximum increase in MRD1 was observed approximately 2 hours post dose in both studies. The MRD1 increase continued through 8 hours post dose.

12.3 Pharmacokinetics

Absorption
The pharmacokinetics of oxymetazoline was evaluated in 24 healthy adult subjects following single-drop administration of UPNEEQ to each eye. The total dose of oxymetazoline HCl was 0.07 mg. Following ocular administration of UPNEEQ, the time to reach peak oxymetazoline concentration (Tmax) values ranged from 0.5 to 12 hours with a median Tmax of 2 hours. The oxymetazoline mean ± standard deviation (SD) peak concentration (Cmax) and area under the concentration-time curve (AUCinf) were 30.5 ± 12.7 pg/mL and 468 ±214 pg*hr/mL, respectively.

Distribution
An in vitro study demonstrated that oxymetazoline is 56.7% to 57.5% bound to human plasma proteins.

Elimination
The oxymetazoline mean terminal half-life (t½) following administration of UPNEEQ in healthy adult subjects is 8.3 hours and ranged from 5.6 to 13.9 hours.

Metabolism
In vitro studies using human liver microsomes showed that oxymetazoline was minimally metabolized, generating mono-oxygenated and dehydrogenated products of oxymetazoline. The percentage of parent drug oxymetazoline remaining was 95.9% after a 120-minute incubation with human liver microsomes.

Excretion
The excretion of oxymetazoline following administration of UPNEEQ has not been characterized in humans.

13 NONCLINICAL TOXICOLOGY

13.1 Carcinogenesis, Mutagenesis, Impairment of Fertility

Carcinogenesis
Oxymetazoline hydrochloride was not associated with an increased incidence of neoplastic or proliferative changes in transgenic mice given oral doses of 0.5, 1.0, or 2.5 mg/kg/day oxymetazoline hydrochloride for 6 months.

Mutagenesis
Oxymetazoline hydrochloride revealed no evidence of mutagenic or clastogenic potential based on the results of two in vitro genotoxicity tests (Ames assay and human lymphocyte chromosomal aberration assay) and one in vivo gentoxicity test (mouse micronucleus assay).

Impairment of Fertility
Effects on fertility and early embryonic development were evaluated in rats following oral administration of 0.05, 0.1, or 0.2 mg/kg/day oxymetazoline hydrochloride prior to and during mating and through early pregnancy. Decreased number of corpora lutea and increased post-implantation losses were noted at 0.2 mg/kg/day oxymetazoline hydrochloride (28 times the MRHOD, on a dose comparison basis). However, no treatment related effects on mating parameters were noted at 0.2 mg/kg/day oxymetazoline hydrochloride.

14 CLINICAL STUDIES

UPNEEQ was evaluated for the treatment of acquired blepharoptosis in two randomized, double-masked, vehicle-controlled, parallel-group clinical efficacy trials. Both studies were randomized in an approximate 2:1 ratio of active versus vehicle. Efficacy was assessed with the Leicester Peripheral Field Test (LPFT) (primary) and photographic measurement of Marginal reflex distance 1 (MRD1). The primary efficacy endpoints were ordered in a hierarchy to compare UPNEEQ to vehicle on the mean increase from baseline (Day 1 Hour 0) in number of points seen on the top 4 rows of the LPFT in the study eye at Hour 6 on Day 1 and Hour 2 on Day 14.

In Trial 1, a total of 140 subjects were randomized 94 patients to the UPNEEQ group and 46 patients to the vehicle group. Treatments were administered once daily to each eye for 42 days (6 weeks). The mean age of the subjects was 64 years. In Trial 2, a total of 164 subjects were randomized 109 patients to the UPNEEQ group and 55 patients to the vehicle group. Treatments were administered once daily to each eye for 42 days (6 weeks). The mean age of the subjects was 63 years.

In both trials, each patient had a designated study eye. The increases in the number of points seen in the superior visual field in the study eye of the UPNEEQ group compared to the vehicle group were statistically significant at both time points, showing that the improvement in superior visual field was evident at the 2-hour time point and maintained at the 6-hour time point. The results from both trials on the primary endpoint are presented below.

Observed and Change from Baseline in Mean Points Seen in Superior Visual Field on LPFT in the Study Eye at Primary Efficacy Time Points (ITT Population)

CL = confidence limit; LPFT = Leicester Peripheral Field Test; ITT (intent-to-treat) – included all randomized subjects
who received at least one dose of study medication; SD = standard deviation
a p-value and 95% CI were based on ANCOVA model adjusted for baseline LFPT points.

Marginal reflex distance 1 (MRD1), showed a positive effect with UPNEEQ treatment. Greater MRD1 increases were observed for the UPNEEQ group than the vehicle group on day 1 at 6 hours post dose and on day 14 at 2 hours post dose.

16 HOW SUPPLIED/STORAGE AND HANDLING

UPNEEQ (oxymetazoline hydrochloride ophthalmic solution), 0.1% is an aseptically prepared, sterile, non-preserved, clear, colorless to slightly yellow ophthalmic solution; 0.3 mL fill in a clear, low-density polyethylene, single patient-use container in a child-resistant foil pouch.

NDC 73687-062-32 Carton of 30 single patient-use containers in individual child-resistant foil pouches.

Storage: Store at 20°C to 25°C (68°F to 77°F). Protect from excessive heat. Keep out of reach of children.

Store single patient-use containers in the child-resistant foil pouches. Opened containers should be discarded immediately after use.

17 PATIENT COUNSELING INFORMATION

Advise the patient and/or caregiver to read the FDA-approved patient labeling (Instructions for Use).

When to Seek Medical Care

- Ptosis may be associated with neurologic or orbital diseases such as stroke and/or cerebral aneurysm, Horner syndrome, myasthenia gravis, external ophthalmoplegia, orbital infection and orbital masses. Consideration should be given to these conditions in the presence of ptosis with decreased levator muscle function and/or other neurologic signs [see Warnings and Precautions (5.1)].
- Alpha-adrenergic agonists as a class may impact blood pressure. Advise patients with cardiovascular disease, orthostatic hypotension, and/or uncontrolled hypertension or hypotension to seek medical care if their condition worsens [see Warnings and Precautions (5.2)].
- Use with caution in patients with cerebral or coronary insufficiency or Sjögren’s syndrome and advise patients to seek medical care if signs and symptoms of potentiation of vascular insufficiency develop [see Warnings and Precautions (5.3)].
- Advise patients to seek immediate medical care if signs and symptoms of acute narrow-angle glaucoma develop [see Warnings and Precautions (5.4)].

Administration Instructions
Use with Contact Lenses
Advise patients that contact lenses should be removed prior to administration of UPNEEQ and can be re-inserted 15 minutes following administration [see Dosage and Administration (2)].

Use with Other Ophthalmic Drugs
If more than one topical ophthalmic drug is being used, the drugs should be administered at least 15 minutes between applications.

Administration
Advise patients that the solution from one single patient-use container is to be used immediately after opening to dose one or both eye(s). The single patient-use container, including any remaining contents, should be discarded immediately after administration [see Dosage and Administration (2)].

Storage and Handling Instructions
Handling the Single Patient-Use Container
Advise patients not to touch the tip of the single patient-use container to their eye or to any surface, in order to avoid eye injury or contamination of the solution.

Storage Information
Instruct patients to keep the single patient-use containers in the child-resistant foil pouches until ready to use. Keep out of reach of children.

To report SUSPECTED ADVERSE REACTIONS, contact RVL Pharmaceuticals, Inc. at 1-877-482-3788 or FDA at 1-800-FDA-1088 or www.fda.gov/medwatch.

© 2025 RVL Pharmaceuticals, Inc. All rights reserved.
Bridgewater, New Jersey 08807
Patents 8357714, 9867808, 10799481, 10814001, 10898573, 10912765, 10940138, 11103482, 11311515, 11324722, 11541036, and 11701343

Made in the U.S.A.
Manufactured for:
RVL Pharmaceuticals, Inc.
PLR-UPN-00007-9
IC # 2284

INSTRUCTIONS FOR USE

UPNEEQ® (up-NEEK)
(oxymetazoline hydrochloride ophthalmic solution), 0.1%
for topical ophthalmic use

Read this Instructions for Use before you start using UPNEEQ and each time you get a refill. There
may be new information. This leaflet does not take the place of talking to your healthcare provider
about your medical condition or your treatment.

UPNEEQ single patient-use container after removal from its individual child-resistant foil pouch

Important Information You Need to Know Before Using UPNEEQ

- UPNEEQ is for use in the eye.
- UPNEEQ can be harmful if swallowed.
- UPNEEQ is supplied as single patient-use containers individually packaged in a child-resistant foil pouch. Do not remove a single patient-use container from the child-resistant foil pouch until you are ready to use UPNEEQ.
- Wash your hands before each use to make sure you do not infect your eyes while using UPNEEQ.
- If you are using UPNEEQ with other eye (ophthalmic) medicines, you should wait at least 15 minutes between using UPNEEQ and the other medicines.
- If you wear contact lenses, remove them before using UPNEEQ. You should wait at least 15
  minutes before placing them back into your eyes.

Using UPNEEQ

- Do not let the tip of the UPNEEQ single patient-use container touch your eye or any other surfaces to avoid contamination or injury to your eye.
- Use 1 drop of UPNEEQ in the affected eye 1 time each day.
- Each single patient-use container of UPNEEQ will give you enough medicine to treat both eyes 1 time each day if needed.
- There is some extra UPNEEQ in each single patient-use container in case you miss getting the drop into your eye.

Storing UPNEEQ

- Store UPNEEQ at room temperature between 68°F to 77°F (20°C to 25°C).
- Store UPNEEQ single patient-use containers in the child-resistant foil pouches they come in.
- Protect UPNEEQ from excessive heat.
- Keep UPNEEQ and all medicines out of the reach of children.

Disposing of UPNEEQ

- After you have applied the daily dose of medicine, throw away (dispose of) the single patient-use container and any unused UPNEEQ.
- Do not save any unused UPNEEQ.

Follow Step 1 to Step 11 each time you use UPNEEQ:

Step 1. Remove 1 UPNEEQ child-resistant foil-pouch from the carton.

Step 2. Make sure the single patient-use container within the foil is moved completely away from the dotted line (see Figure A).

Step 3. Cut the foil along the dotted line using scissors (see Figure B).

Figure A

Figure B

Step 4. Remove the single patient-use container from the foil pouch and then hold it by the long flat end (see Figure C).

Figure C

Step 5. Hold the single patient-use container upright and tap the top of the container gently to make sure that the medicine is in the bottom part of the container (see Figure D).

Figure D

Step 6. Open the single patient-use container by twisting off the tab (see Figure E).

Do not let the tip of the container touch your eye or any other surfaces.

Figure E

Step 7. Tilt your head backwards. If you are not able to tilt your head, lie down.

Step 8. Gently pull your lower eyelid downwards and look up (see Figure F).

Figure F

Step 9. Place the tip of the single patient-use container close to your eye, but be careful not to touch your eye with it (see Figure G).

Step 10. Gently squeeze the single patient-use container and let 1 drop of UPNEEQ fall into the space between your lower eyelid and your eye (see Figure G). If a drop misses your eye, try again.

Figure G

Step 11. Repeat Step 7 to Step 10 for your other eye if instructed to do so by your healthcare provider.

There is enough UPNEEQ in one container for both eyes if needed.

- After you have applied the daily dose of UPNEEQ, throw away the opened single patient-use container with any remaining medicine.
- Be sure to keep this medicine away from children.
- If you use contact lenses, wait at least 15 minutes before placing them back into your eyes.

Manufactured for:
RVL Pharmaceuticals, Inc.
Bridgewater, NJ 08807
1-877-482-3788
PLR-UPN-00007-9

This Instruction for Use has been approved by the U.S. Food and Drug Administration.
Approved: August 2020

PRINCIPAL DISPLAY PANEL

UPNEEQ 30ct Trade Carton

NDC: 73687-062-32

PRINCIPAL DISPLAY PANEL

UPNEEQ Trade Foil Pouch

NDC: 73687-062-70

Upneeq Trade Foil Rev. 112021